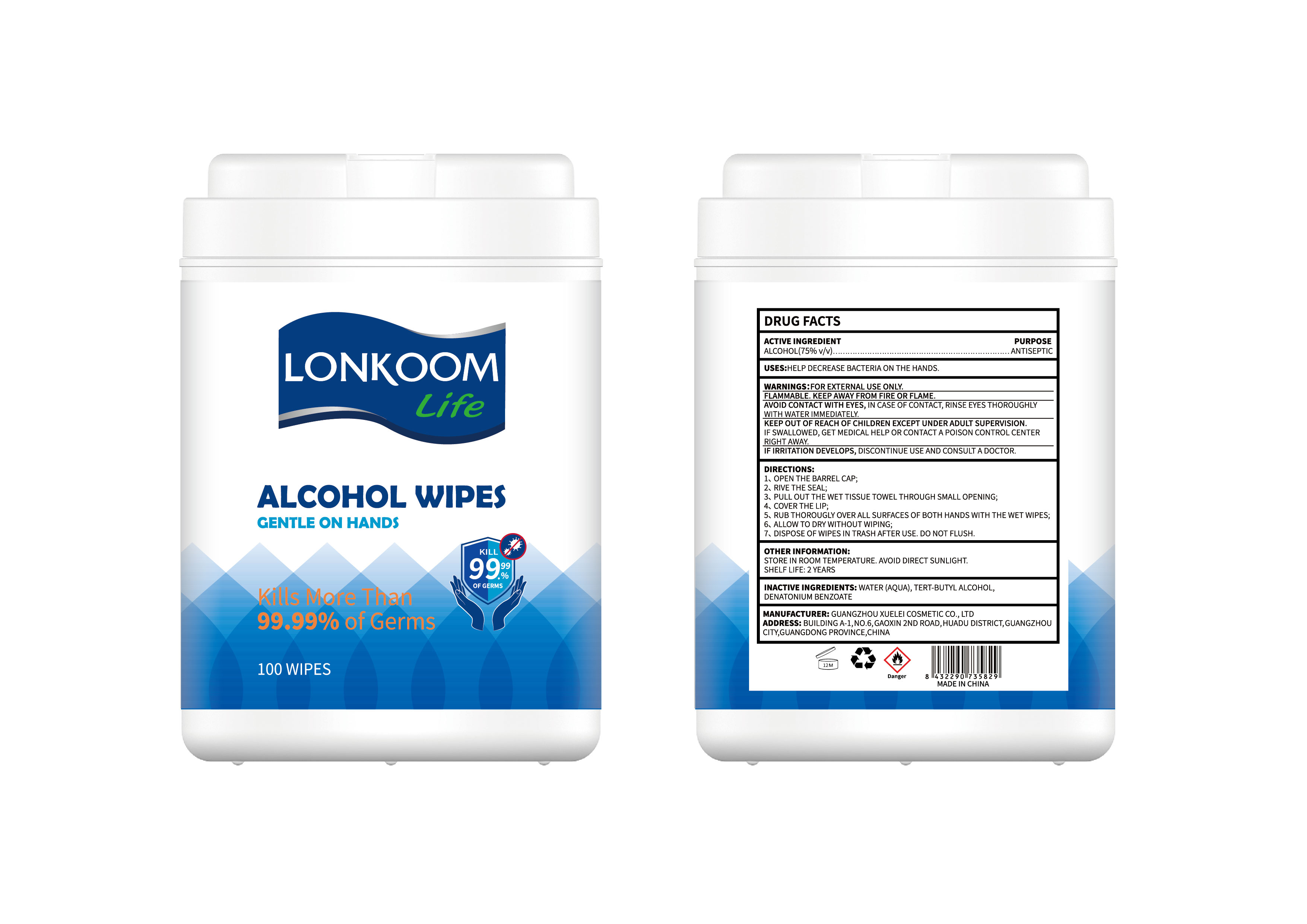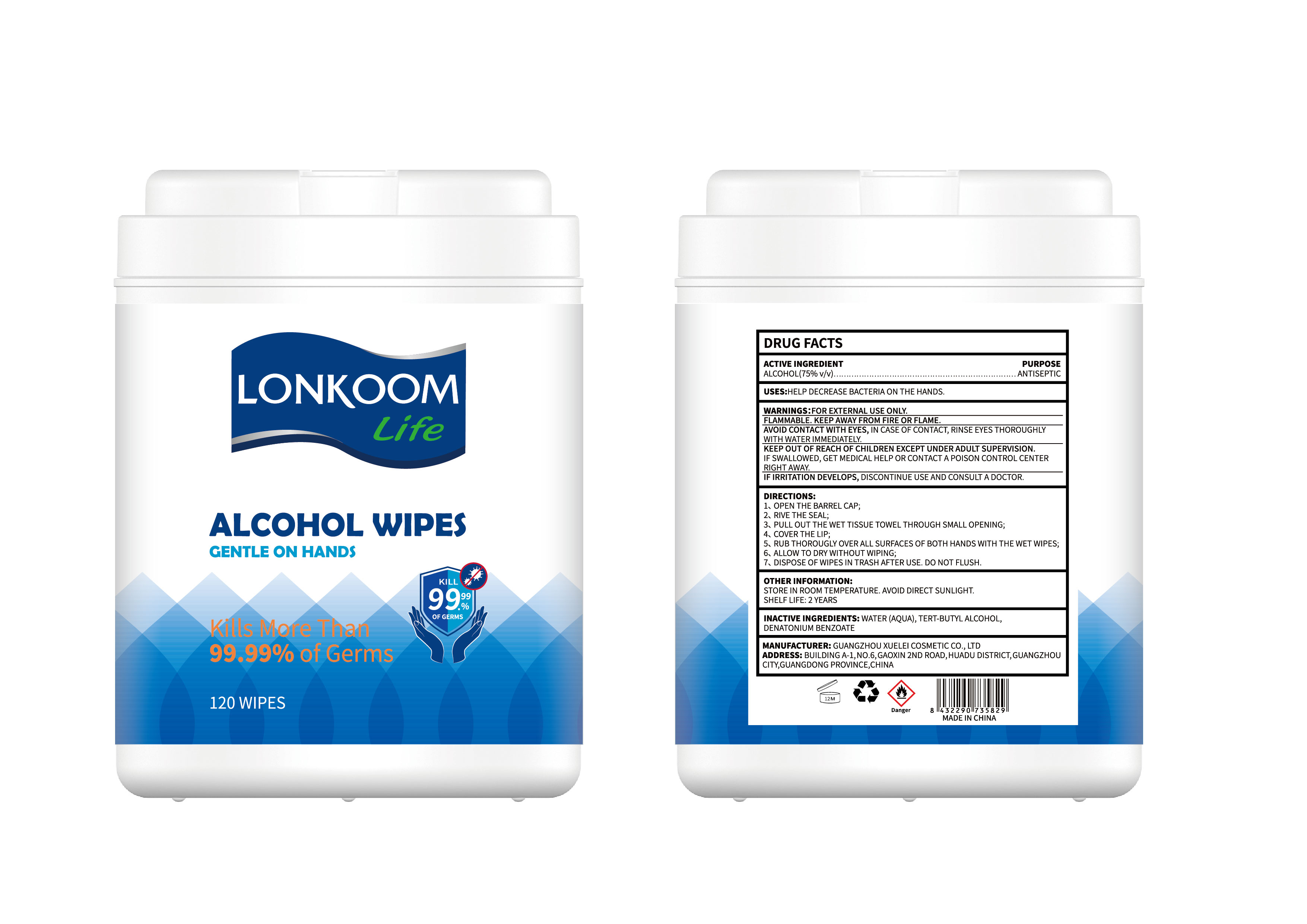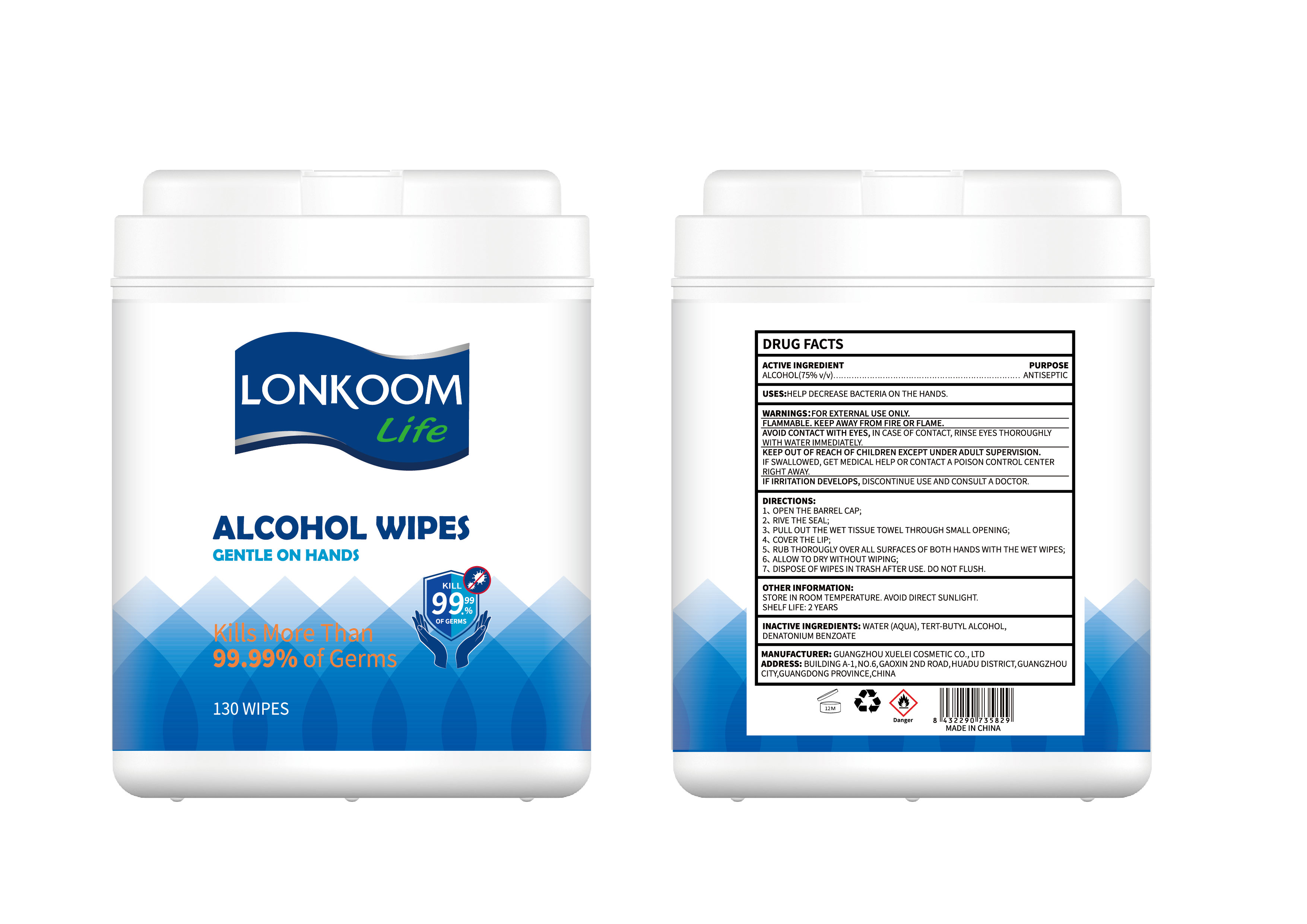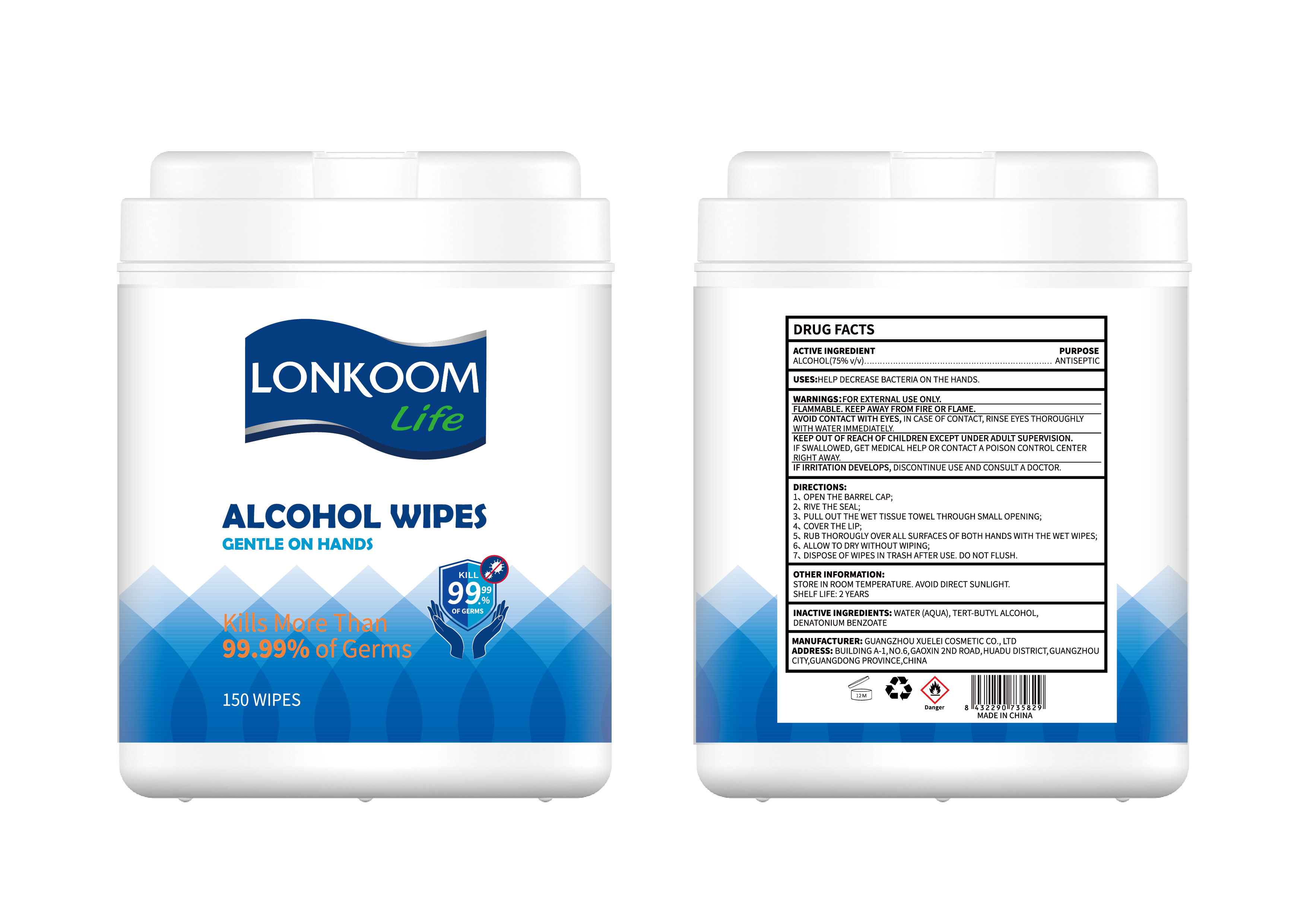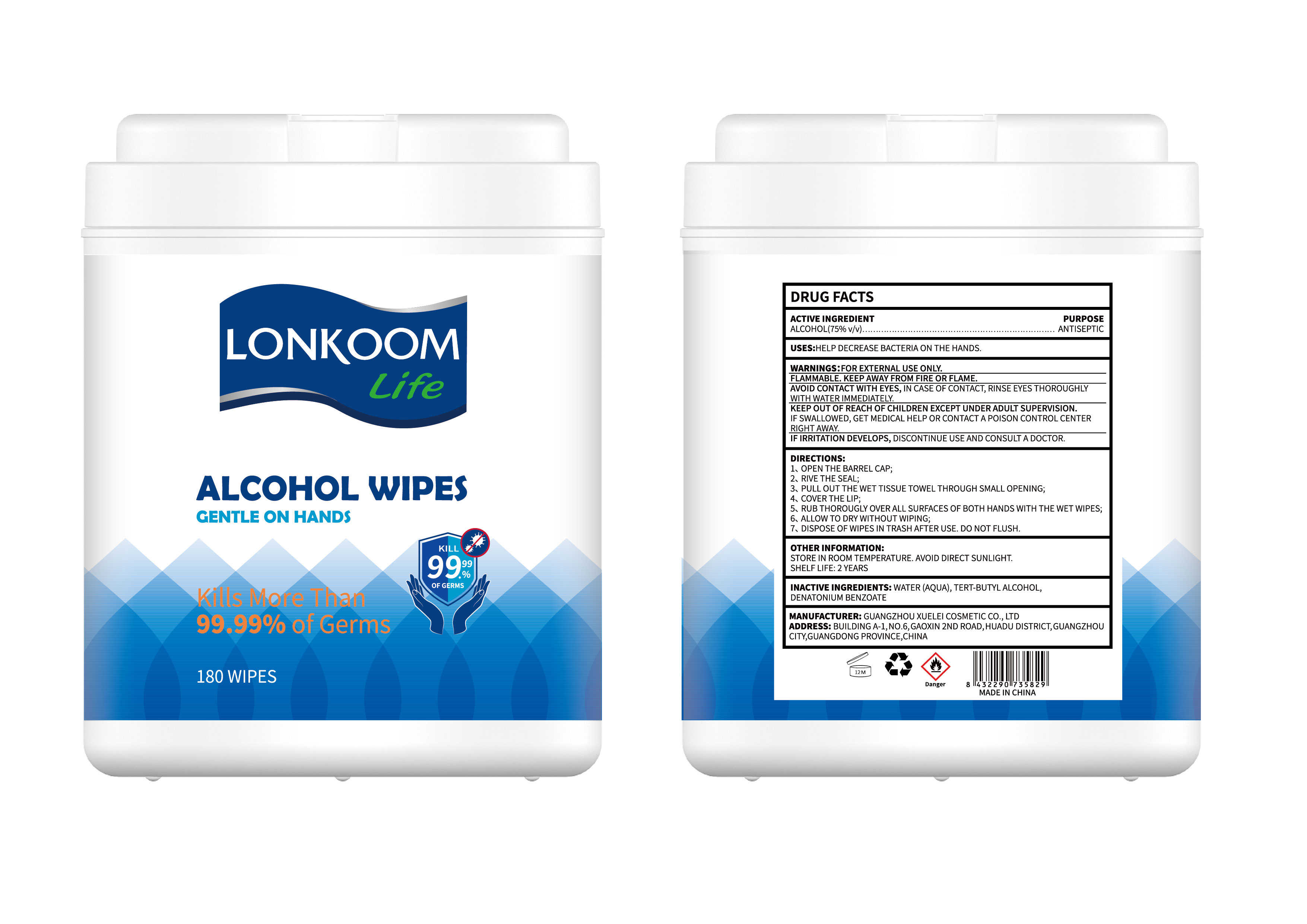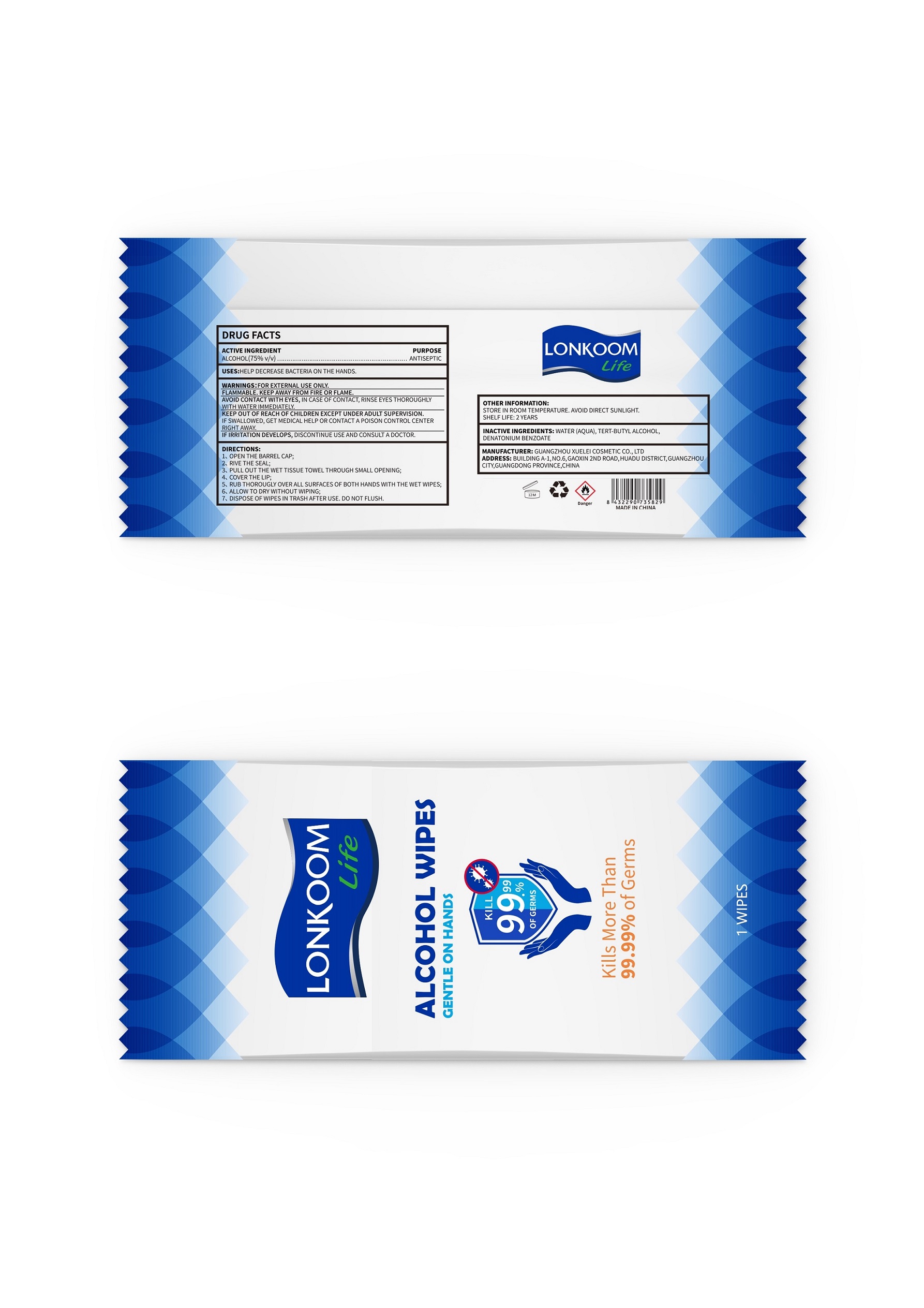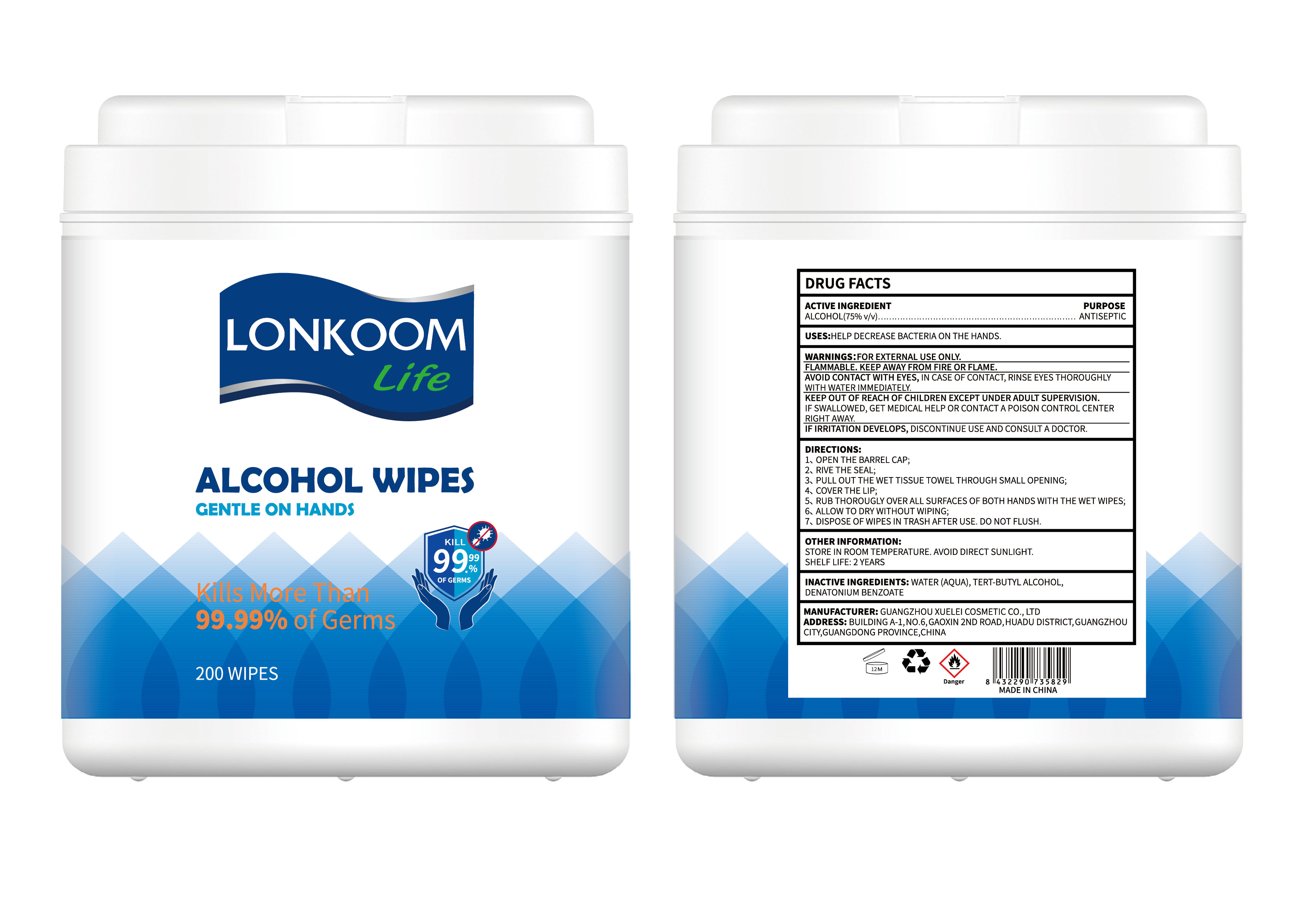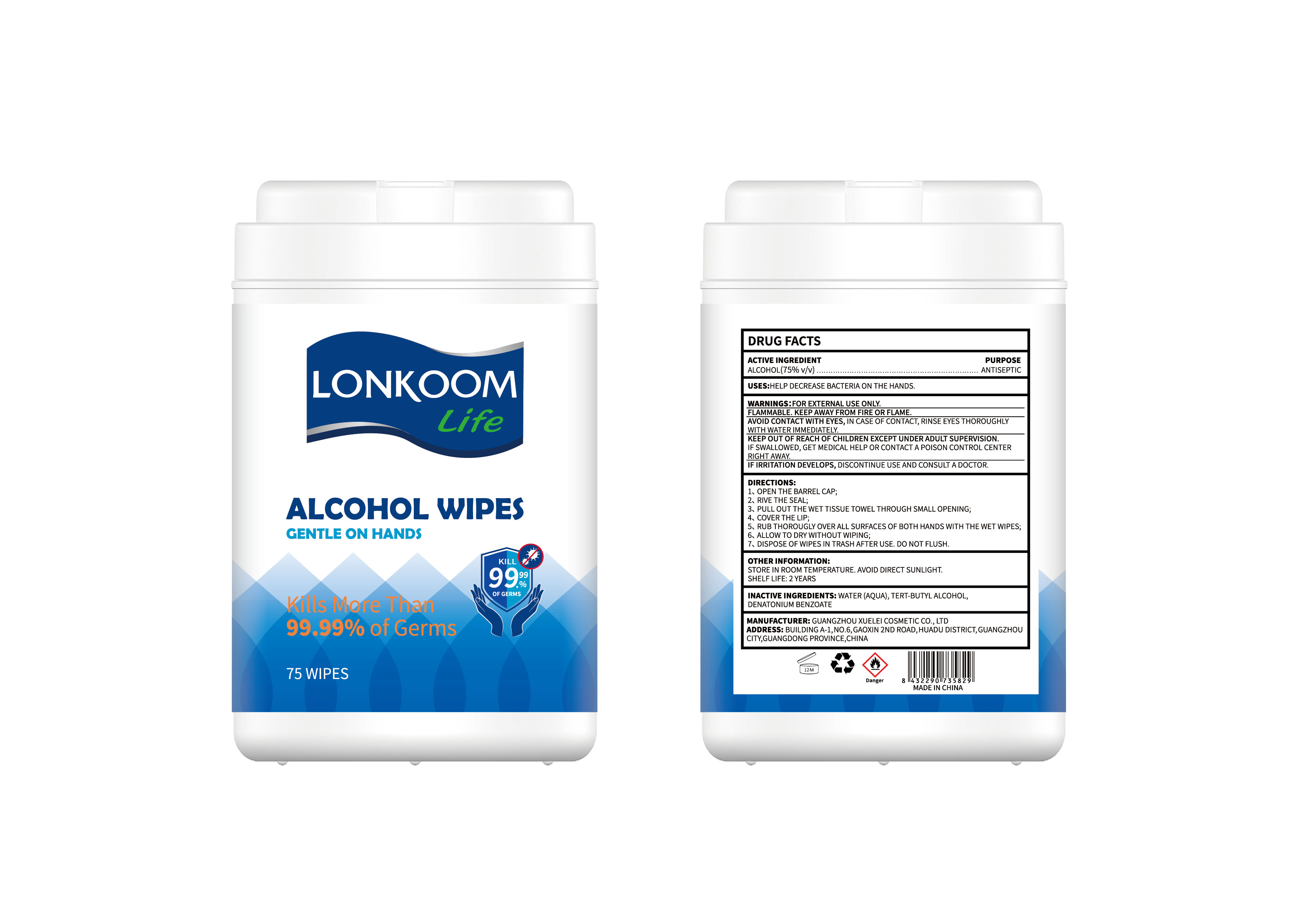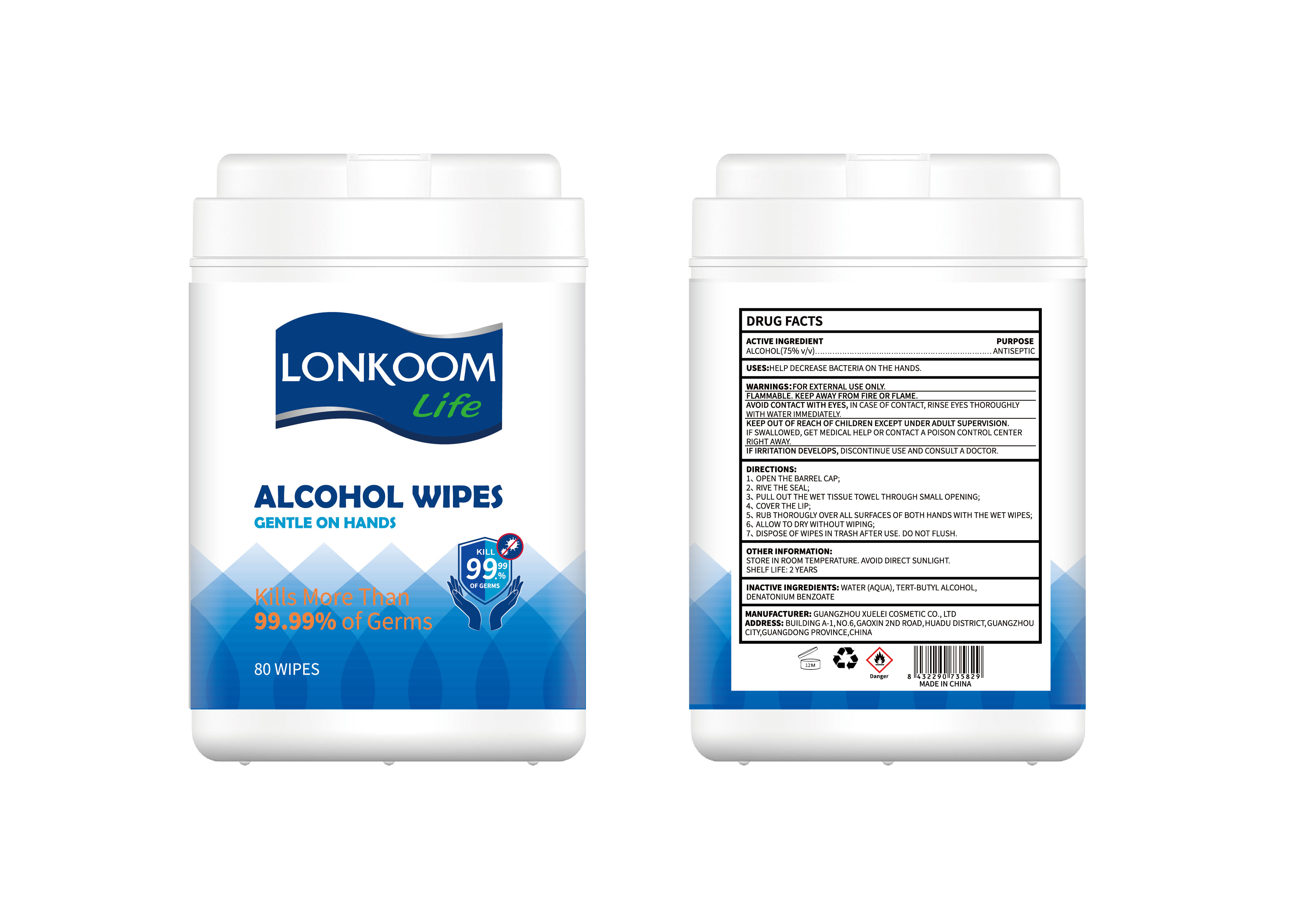 DRUG LABEL: ALCOHOL WIPES
NDC: 74658-013 | Form: CLOTH
Manufacturer: GUANGZHOU XUELEI COSMETIC CO.,LTD.
Category: otc | Type: HUMAN OTC DRUG LABEL
Date: 20211110

ACTIVE INGREDIENTS: ALCOHOL 75 mL/100 mL
INACTIVE INGREDIENTS: TERT-BUTYL ALCOHOL; WATER; DENATONIUM BENZOATE ANHYDROUS

ALCOHOL WIPES

ACTIVE INGREDIENT

ALCOHOL (75% v/v)

PURPOSE

ANTISEPTIC

USES

HELP DECREASE BACTERIA ON THE HANDS.

WARNINGS

FOR EXTERNAL USE ONLY.

FLAMMABLE. KEEP AWAY FROM FIRE OR FLAME.

AVOID CONTACT WITH EYES, IN CASE OF CONTACT, RINSE EYES THOROUGHLY WITH WATER IMMEDIATELY.

KEEP OUT OF REACH OF CHILDREN EXCEPT UNDER ADULT SUPERVISION.

IF SWALLOWED, GET MEDICAL HELP OR CONTACT A POISON CONTROL CENTER RIGHT AWAY.

IF IRRITATION DEVELOPS, DISCONTINUE USE AND CONSULT A DOCTOR.

KEEP OUT OF REACH OF CHILDREN EXCEPT UNDER ADULT SUPERVISION.

DIRECTIONS

1、OPEN THE BARREL CAP;

2、RIVE THE SEAL;

3、PULL OUT THE WET TISSUE TOWEL THROUGH SMALL OPENING;

4、COVER THE LIP;

5、RUB THOROUGHLY OVER ALL SURFACES OF BOTH HANDS WITH THE WET WIPES;

6、ALLOW TO DRY WITHOUT WIPING;

7、DISPOSE OF WIPES IN TRASH AFTER USE. DOT NOT FLUSH.

OTHER INFORMATION

STORE IN ROOM TEMPERATURE. AVOID DIRECT SUNLIGHT.

SHELF LIFE: 2 YEARS

INACTIVE INGREDIENTS

WATER (AQUA), TERT-BUTYL ALCOHOL, DENATONIUM BENZOATE

PACKAGE LABEL

1 WIPES, NDC: 74658-013-01

75 WIPES, NDC: 74658-013-02

80 WIPES, NDC: 74658-013-03

100 WIPES, NDC: 74658-013-04

120 WIPES, NDC: 74658-013-05

130 WIPES, NDC: 74658-013-06

150 WIPES, NDC: 74658-013-07

180 WIPES, NDC: 74658-013-08

200 WIPES, NDC: 74658-013-09